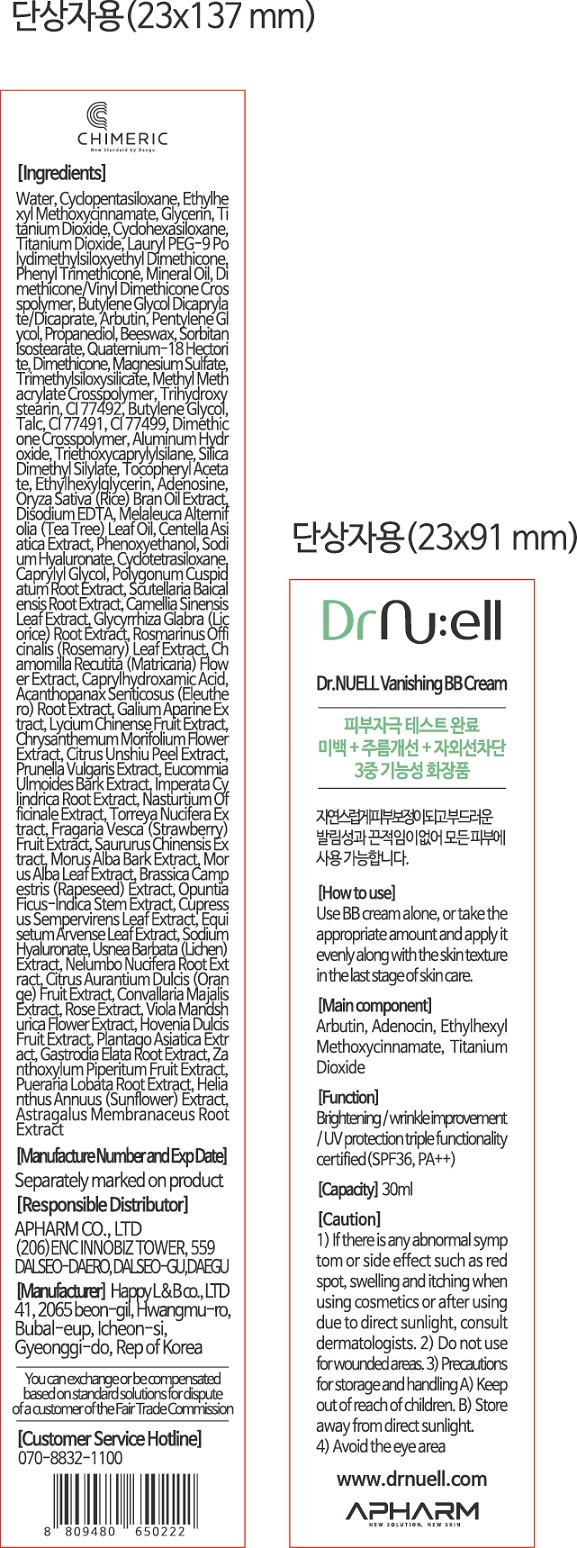 DRUG LABEL: Dr.NUELL Vanishing BB
NDC: 73430-0007 | Form: CREAM
Manufacturer: Apharm Co., Ltd.
Category: otc | Type: HUMAN OTC DRUG LABEL
Date: 20191110

ACTIVE INGREDIENTS: GLYCERIN 7 g/100 mL; ADENOSINE 0.04 g/100 mL
INACTIVE INGREDIENTS: PROPANEDIOL; BUTYLENE GLYCOL

ACTIVE INGREDIENT

arbutin, adenosine, ethylhexyl methoxycinnamate, titanium dioxide

PURPOSE

brightening

wrinkle improvement

UV protection

Keep out of reach of children

INDICATIONS AND USAGE

use BB cream alone, or take the appropriate amount and apply it evenly along with the skin texture in the last stage of skin care

WARNINGS

1) if there is any abnormal symptom or side effect, such as red spot, swelling and itching when using cosmetlcs or after using due to direct sunlight, consult dermatologists
2) Do not use for wounded areas
3) Precautions for storage and handling
keep out of reach of children, store away from direct sunlight
4) avoid the eye area

INACTIVE INGREDIENT

water, cyclopentasiloxane, dimethicone, etc.

DOSAGE AND ADMINISTRATION

For external use only